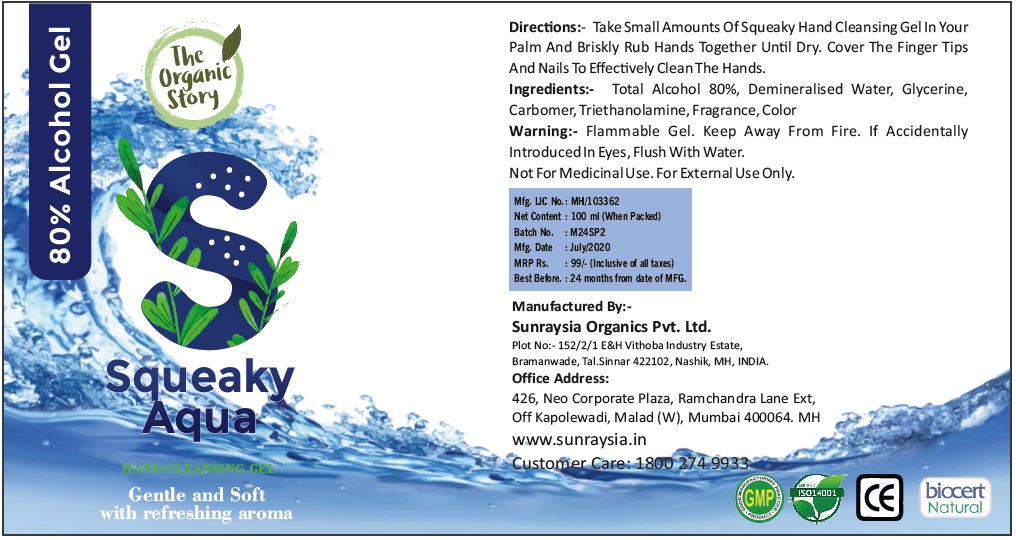 DRUG LABEL: Squeaky Aqua Hand Sanitizing Gel
NDC: 80288-024 | Form: GEL
Manufacturer: SUNRAYSIA ORGANICS PRIVATE LIMITED
Category: otc | Type: HUMAN OTC DRUG LABEL
Date: 20200903

ACTIVE INGREDIENTS: ALCOHOL 80 mL/100 mL
INACTIVE INGREDIENTS: WATER; GLYCERIN; CARBOMER HOMOPOLYMER, UNSPECIFIED TYPE; TROLAMINE

The Organic Story Squeaky Aqua HAND CLEANSING GEL

Active Ingredient:- Total Alcohol 80%

Purpose:- Antiseptic

INDICATIONS AND USAGE

Use:- Hand Sanitizer To Decrease Bacteria On The Skin

DOSAGE AND ADMINISTRATION

Directions:- Take Small Amounts Of Squeaky Hand Cleansing Gel In Your Palm And Briskly Rub Hands

Together Until Dry. Cover The Finger Tips And Nails To Effectively Clean The Hands.

INACTIVE INGREDIENT

Ingredients:- Total Alcohol 80%, Demineralised Water, Glycerine, Carbomer, Triethanolamine, Fragrance, Color

WARNINGS

Warning:- Flammable Gel. Keep Away From Fire. If Accidentally Introduced In Eyes, Flush With Water.

Not For Medicinal Use. For External Use Only.

Keep Out Of Reach Of Children.

The Organic Story

Gentle and Soft with refreshing aroma

Manufactured By:-

Sunraysia Organics Pvt. Ltd.

Plot No:- 152/2/1 E&H Vithoba Industry Estate,

Bramanwade, Tal.Sinnar 422102, Nashik, MH, INDIA.

Office Address:

426, Neo Corporate Plaza, Ramchandra Lane Ext,

Off Kapolewadi, Malad (W), Mumbai 400064. MH

www.sunraysia.in

Customer Care: 1800 274 9933

GMP

ISO14001

biocert Natural